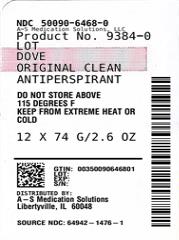 DRUG LABEL: Dove
NDC: 50090-6468 | Form: STICK
Manufacturer: A-S Medication Solutions
Category: otc | Type: HUMAN OTC DRUG LABEL
Date: 20250114

ACTIVE INGREDIENTS: ALUMINUM CHLOROHYDRATE 20 g/100 g
INACTIVE INGREDIENTS: CYCLOMETHICONE 5; ISOPROPYL PALMITATE; STEARYL ALCOHOL; MINERAL OIL; TALC; HYDROGENATED CASTOR OIL; SUNFLOWER OIL; STEARETH-100; BUTYLATED HYDROXYTOLUENE

Dove Original Clean 24h Invisible Solid Antiperspirant Deodorant

Active ingredient

Aluminum Chlorohydrate (20%)

Purpose

anti-perspirant

Uses

- reduces underarm wetness
- 24 Hour Protection

Warnings

For external use only
Do not use on broken skin
Ask a doctor before use if you have kidney disease
Stop use if rash or irritation occurs

Keep out of reach of children.

If swallowed, get medical help or contact a Poison Control Center right away.

Directions

apply to underarms only

Inactive Ingredients

Cyclopentasiloxane, Isopropyl Palmitate, Stearyl Alcohol, Mineral Oil, Talc, Hydrogenated Castor Oil, Fragrance (Parfum), Helianthus Annuus (Sunflower) Seed Oil, Steareth-100, BHT.

Questions?

Call tollfree 1-800-761-3683

HOW SUPPLIED

Product: 50090-6468

NDC: 50090-6468-0 74 g in a CONTAINER / 12 in a CASE